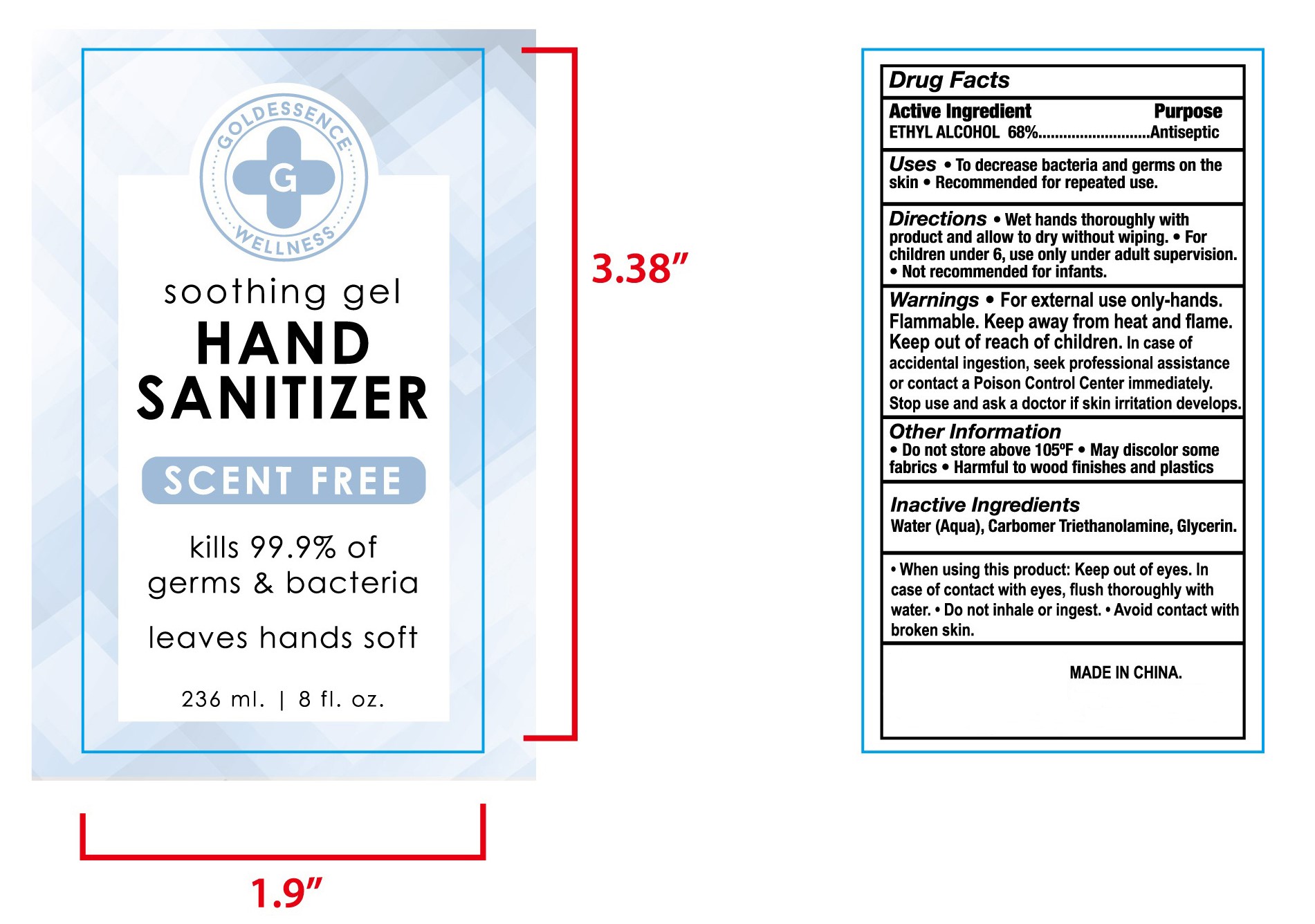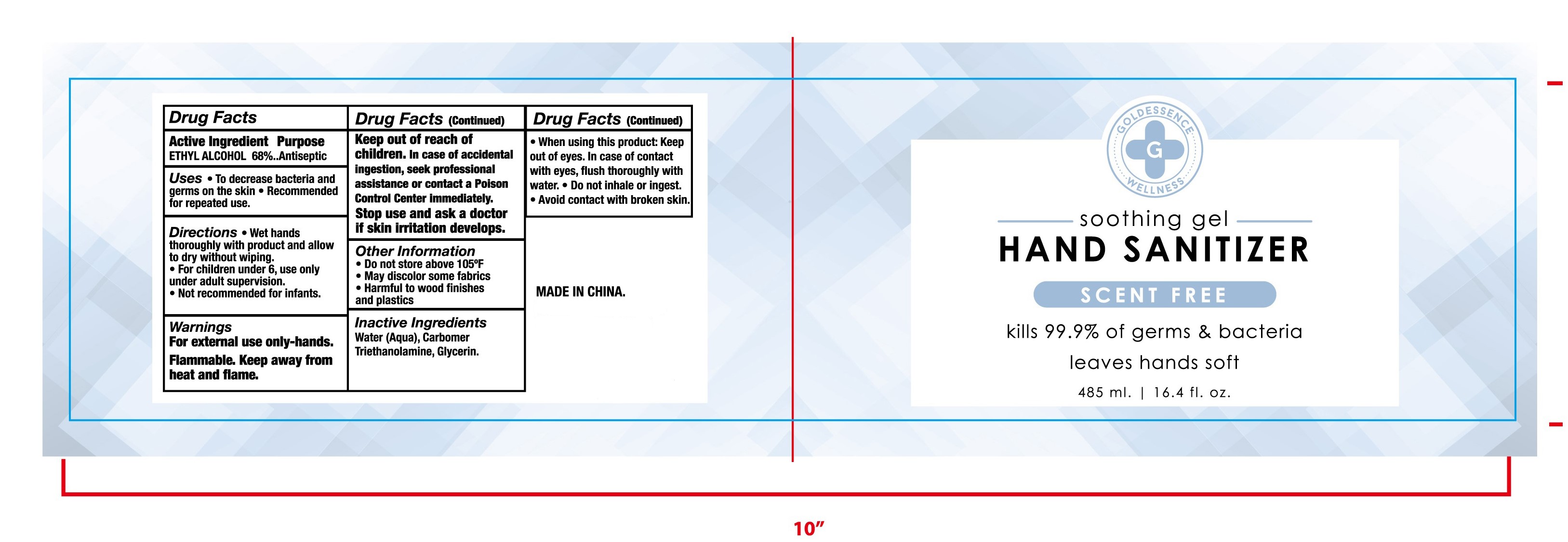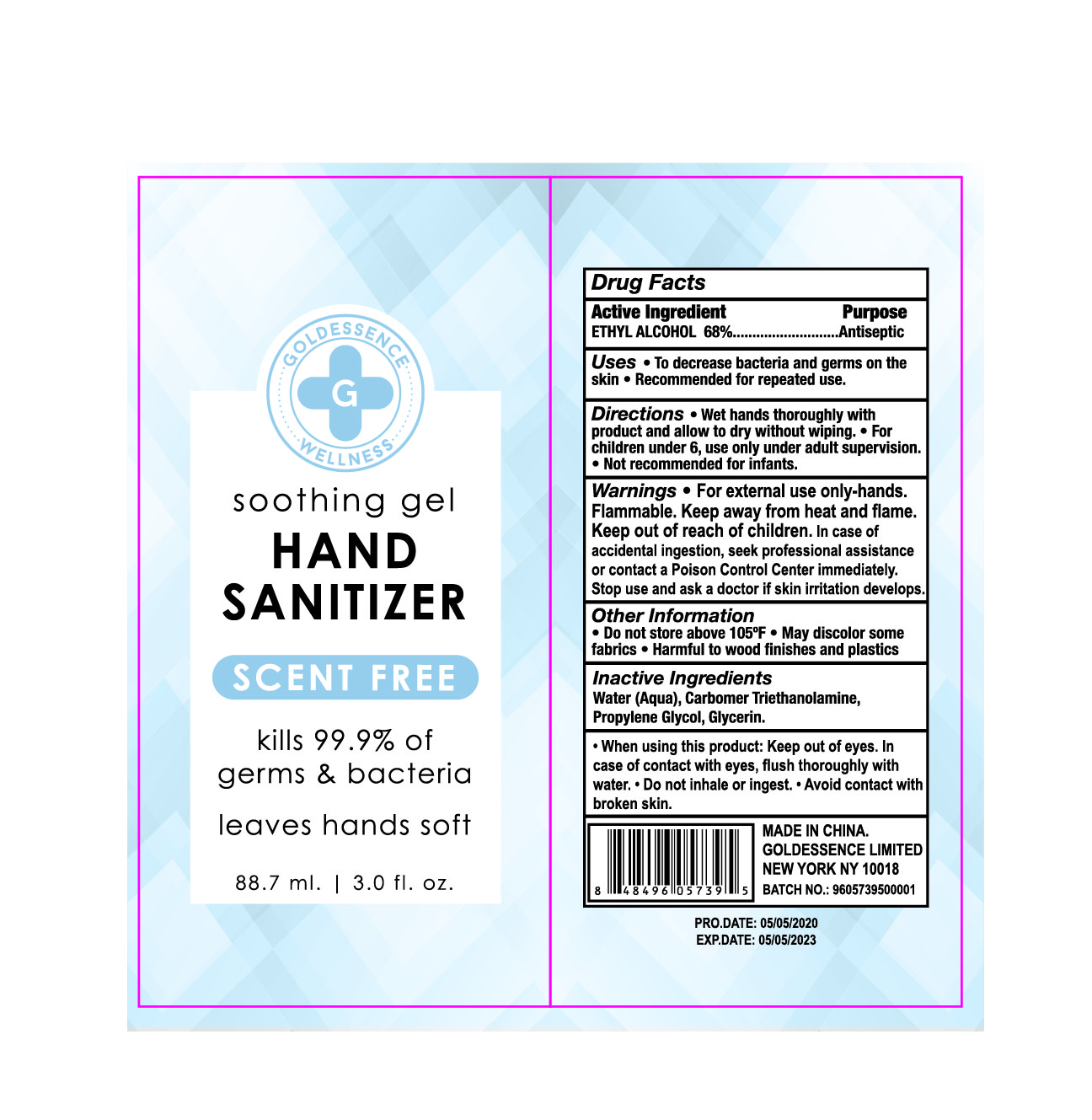 DRUG LABEL: HAND SANITIZER
NDC: 47993-222 | Form: GEL
Manufacturer: NINGBO JIANGBEI OCEAN STAR TRADING CO.,LTD
Category: otc | Type: HUMAN OTC DRUG LABEL
Date: 20201103

ACTIVE INGREDIENTS: ALCOHOL 68 g/112 mL
INACTIVE INGREDIENTS: WATER 14 g/112 mL; CARBOMER 940 12 g/112 mL; TRIETHANOLAMINE BENZOATE 3 g/112 mL; GLYCERIN 2 g/112 mL; ALOE VERA LEAF 1 g/112 mL

47993-222

Active ingredients

Ethyl Alcohol 68%

PURPOSE

Antiseptic

Warnings:

For external use only-hands.Flammable.Keep away from heat and flame

ASK DOCTOR

In case of accidental ingestion, seek professional assistance or contact a Poison Control Center immediately

Stop use and ask a doctor if skin irritation develops.

Uses：

To decrease bacteria and germs on the skin.
Recommended for repeated use.

Directions:

Wet hands thoroughly with product and allow to dry without wiping.
For children under 6,use only under adult supervision.
Not recommended for infants.

Keep out of reach of children. For children under 6,use only under adult supervision.

OTHER SAFETY INFORMATION

Do not store above 105℉
May discolor some fabrics
Harmful to wood finishes and plastics

INACTIVE INGREDIENT

Do not store above 105℉
May discolor some fabrics
Harmful to wood finishes and plastics